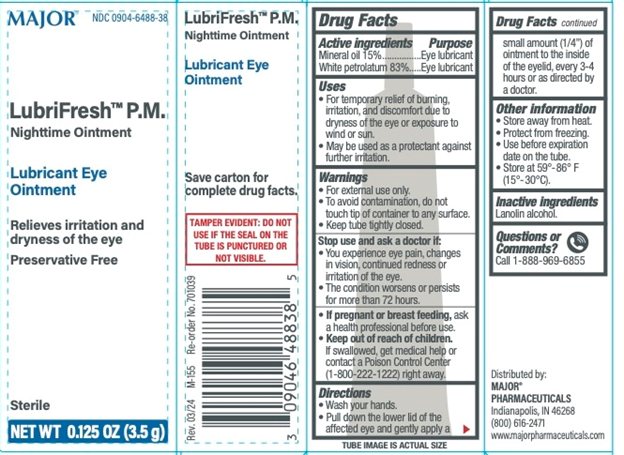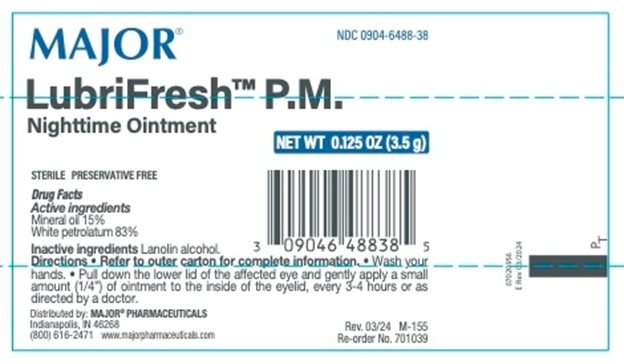 DRUG LABEL: Major LubriFresh PM
NDC: 0904-6488 | Form: OINTMENT
Manufacturer: Major Pharmaceuticals
Category: otc | Type: HUMAN OTC DRUG LABEL
Date: 20250905

ACTIVE INGREDIENTS: MINERAL OIL 150 mg/1 g; PETROLATUM 830 mg/1 g
INACTIVE INGREDIENTS: LANOLIN ALCOHOLS

Major Lubrifresh P.M.

Active ingredients Purpose

Mineral oil 15%...................................................Lubricant

White petrolatum 83%.........................................Lubricant

Uses

- For the temporary relief of burning, irritation, and discomfort due to dryness of the eye or exposure to wind or sun
- May be used as a protectant against further irritation

Warnings

- For external use only.
- To avoid contamination, do not touch tip of container to any surface
- Keep tube tightly closed

Stop use and ask a doctor if

- You experience eye pain, changes in vision, continued redness or irritation of the eye
- The condition worsens or persists more than 72 hours

- If pregnant or breast feeding, ask a health professional before use.

Keep out of reach of children

If swallowed, get medical help or contact a Poison Control Center (1-800-222-1222) right away.

Directions

- Wash your hands.
- Pull down the lower lid of the affected eye(s) and gently apply a small amount (1/4") of ointment to the inside of the eyelid, every 3-4 hours or as directed by a doctor.

Other information

- Store away from heat
- Protect from freezing
- Use before expiration date marked on container
- Store at 59°-86°F (15°-30°C)

Inactive ingredients

Lanolin alcohol

DOSAGE AND ADMINISTRATION

Distributed by:

Major Pharmaceuticals

17177 N Laurel Park Dr.,

Suiet 233

Livonia, MI 48150

Rev. 03/24 | M-155 | Re-order No. 701039

Principal Display Panel - tube

MAJOR®

NDC 0904-6488-38

LubriFresh™ P.M.

Nighttime Ointment

Principal Display Panel - carton

MAJOR®

NDC 0904-6488-38

LubiFresh™ P.M.

Nighttime Ointment

Lubricant Eye

Ointment

Relieves irritation and

dryness of the eye

Preservative Free

Sterile

NET WT 0.125 OZ (3.5 g)